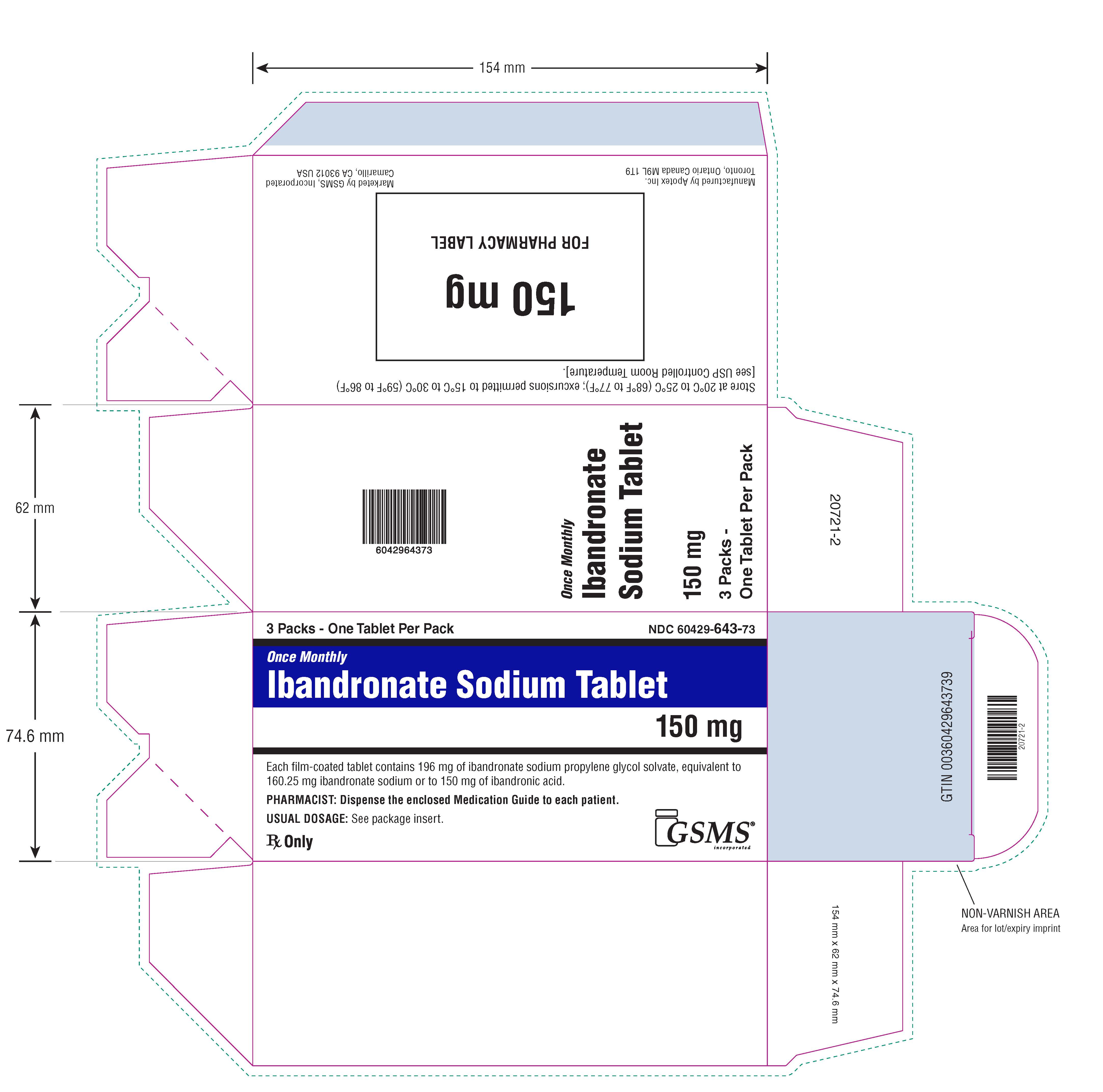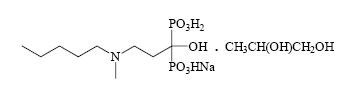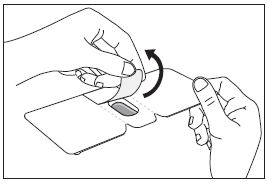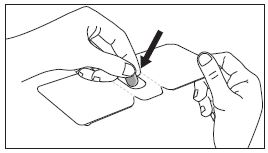 DRUG LABEL: IBANDRONATE SODIUM
NDC: 60429-643 | Form: TABLET, FILM COATED
Manufacturer: Golden State Medical Supply, Inc.
Category: prescription | Type: HUMAN PRESCRIPTION DRUG LABEL
Date: 20260219

ACTIVE INGREDIENTS: IBANDRONATE SODIUM 150 mg/1 1
INACTIVE INGREDIENTS: MICROCRYSTALLINE CELLULOSE; CROSPOVIDONE (120 .MU.M); MAGNESIUM STEARATE; SILICON DIOXIDE; HYPROMELLOSE, UNSPECIFIED; POLYETHYLENE GLYCOL 8000; WATER

HIGHLIGHTS OF PRESCRIBING INFORMATION

IBANDRONATE SODIUM TABLETS. These highlights do not include all the information needed to use IBANDRONATE SODIUM TABLETS safely and effectively. See full prescribing information for IBANDRONATE SODIUM TABLETS.
IBANDRONATE SODIUM tablets, for oral use
Initial U.S. Approval: 2003

RECENT MAJOR CHANGES

Warnings and Precautions, Atypical Fractures Including Femoral Fractures (5.5) 10/2025

1 INDICATIONS AND USAGE

Ibandronate sodium tablet is a bisphosphonate indicated for the treatment and prevention of postmenopausal osteoporosis. (1.1).

Limitations of Use

The optimal duration of use has not been determined. For patients at low -risk for fracture, consider drug discontinuation after 3 to 5 years of use. (1.2).

2 DOSAGE AND ADMINISTRATION

- Take one 150 mg tablet once monthly on the same day each month (2.1)
- Instruct patient to: (2.2)
  - Swallow whole tablet with 6 to 8 oz of plain water only, at least 60 minutes before the first food, beverage, or medication of day. Avoid lying down for at least 60 minutes after taking ibandronate sodium tablets.
  - Do not eat, drink (except for water), or take other medication for 60 minutes after taking ibandronate sodium tablets.
- Take supplemental calcium and vitamin D if dietary intake inadequate (2.3)

3 DOSAGE FORMS AND STRENGTHS

Tablets: 150 mg (3)

4 CONTRAINDICATIONS

- Abnormalities of the esophagus which delay esophageal emptying such as stricture or achalasia (4, 5.1)
- Inability to stand or sit upright for at least 60 minutes (4, 5.1)
- Hypocalcemia (4)
- Hypersensitivity to ibandronate sodium tablets (4)

5 WARNINGS AND PRECAUTIONS

- Upper gastrointestinal Adverse Reactionscan occur. Instruct patients to follow dosing instructions and discontinue use if new or worsening symptoms occur. (5.1)
- Hypocalcemiamay worsen during treatment. Correct hypocalcemia before use. (5.2)
- Severe Bone, Joint, and Muscle Painmay occur. Consider discontinuing use if symptoms develop. (5.3)
- Osteonecrosis of the Jawhas been reported. (5.4)
- Atypical Fracturesincluding Femoral Fractures have been reported. Patients with new thigh or groin pain should be evaluated to rule out a femoral fracture. Risk/benefit of continuing bisphosphonate therapy should be re-evaluated in these patients and interruption of bisphosphonate therapy should be considered. (5.5)

6 ADVERSE REACTIONS

The most common adverse reactions (greater than 5%) are back pain, dyspepsia, pain in extremity, diarrhea, headache, and myalgia. (6)

To report SUSPECTED ADVERSE REACTIONS, contact Apotex Corp. at 1-800-706-5575 or FDA at 1-800-FDA-1088 or www.fda.gov/medwatch.

7 DRUG INTERACTIONS

- Calcium supplements, antacids and some oral medications may interfere with absorption of ibandronate. Do not take within 60 minutes of dosing (7.1)
- Use caution when co-prescribing aspirin/nonsteroidal anti-inflammatory drugs that may worsen gastrointestinal irritation. (7.2)

8 USE IN SPECIFIC POPULATIONS

Ibandronate sodium tablets are not recommended in patients with severe renal impairment (creatinine clearance less than 30 mL/min). (5.6, 8.6)

FULL PRESCRIBING INFORMATION

1 INDICATIONS AND USAGE

1.1 Treatment and Prevention of Postmenopausal Osteoporosis

Ibandronate sodium tablets are indicated for the treatment and prevention of osteoporosis in postmenopausal women. Ibandronate sodium increases bone mineral density (BMD) and reduces the incidence of vertebral fractures.

1.2 Important Limitations of Use

Theoptimalduration of use has not been determined. The safety and effectiveness of ibandronate sodium tablets for the treatment of osteoporosis are based on clinical data of three years duration. All patients on bisphosphonate therapy should have the need for continued therapy re-evaluated on a periodic basis. Patients at low-risk for fracture should be considered for drug discontinuation after 3 to 5 years of use. Patients who discontinue therapy should have their risk for fracture re-evaluated periodically.

2 DOSAGE AND ADMINISTRATION

2.1 Dosage Information

The dose of ibandronate sodium tablet is one 150 mg tablet taken once monthly on the same date each month.

2.2 Important Administration Instructions

Instruct Patients to do the following:

- Take ibandronate sodium tablets at least 60 minutes before the first food or drink (other than water) of the day or before taking any oral medication or supplementation, including calcium, antacids, or vitamins to maximize absorption and clinical benefit, (see DRUG INTERACTIONS [7.1]) . Avoid the use of water with supplements including mineral water because they may have a higher concentration of calcium.
- Swallow ibandronate sodium tablets whole with a full glass of plain water (6 to 8 oz) while standing or sitting in an upright position to reduce the potential for esophageal irritation. Avoid lying down for 60 minutes after taking ibandronate sodium tablets (see WARNINGS AND PRECAUTIONS [5.1]). Do not chew or suck the tablet because of a potential for oropharyngeal ulceration.
- Do not eat, drink anything except plain water, or take other medications for at least 60 minutes after taking ibandronate sodium tablets.

2.3 Recommendations for Calcium and Vitamin D Supplementation

Instruct patients to take supplemental calcium and vitamin D if their dietary intake is inadequate. Avoid the use of calcium supplements within 60 minutes of ibandronate sodium administration because co-administration of ibandronate sodium tablets and calcium may interfere with the absorption of ibandronate sodium (see DRUG INTERACTIONS [7.1]) .

2.4 Administration Instructions for Missed Once-Monthly Doses

If the once-monthly dose is missed, instruct patients to do the following:

- If the next scheduled ibandronate sodium tablet day is more than 7 days away, take one ibandronate sodium 150 mg tablet in the morning following the date that it is remembered.
- If the next scheduled ibandronate sodium tablets day is only 1 to 7 days away, wait until the subsequent month’s scheduled ibandronate sodium tablet day to take their tablet.

For subsequent monthly doses for both of the above scenarios, instruct patients to return to their original schedule by taking one ibandronate sodium 150 mg tablet every month on their previous chosen day.

3 DOSAGE FORMS AND STRENGTHS

Tablets, 150 mg: white to off-white, oval, biconvex, film-coated tablets, engraved with "APO" on one side and "IBA150" on the other side.

4 CONTRAINDICATIONS

Ibandronate sodium tablets are contraindicated in patients with the following conditions:

- Abnormalities of the esophagus which delay esophageal emptying such as stricture or achalasia (see Warnings and Precautions [5.1])
- Inability to stand or sit upright for at least 60 minutes (see Dosage and Administration [2.2], and Warnings and Precautions [5.1])
- Hypocalcemia (see Warnings and Precautions [5.2])
- Known hypersensitivity to ibandronate sodium tablets or to any of its excipients. Cases of anaphylaxis have been reported (see Adverse Reactions [6.2]).

5 WARNINGS AND PRECAUTIONS

5.1 Upper Gastrointestinal Adverse Reactions

Ibandronate sodium tablets, like other bisphosphonates administered orally, may cause local irritation of the upper gastrointestinal mucosa. Because of these possible irritant effects and a potential for worsening of the underlying disease, caution should be used when ibandronate sodium tablets are given to patients with active upper gastrointestinal problems (such as known Barrett's esophagus, dysphagia, other esophageal diseases, gastritis, duodenitis or ulcers).

Esophageal adverse experiences, such as esophagitis, esophageal ulcers and esophageal erosions, occasionally with bleeding and rarely followed by esophageal stricture or perforation, have been reported in patients receiving treatment with oral bisphosphonates. In some cases, these have been severe and required hospitalization. Physicians should therefore be alert to any signs or symptoms signaling a possible esophageal reaction and patients should be instructed to discontinue ibandronate sodium tablets and seek medical attention if they develop dysphagia, odynophagia, retrosternal pain or new or worsening heartburn.

The risk of severe esophageal adverse experiences appears to be greater in patients who lie down after taking oral bisphosphonates and/or who fail to swallow it with the recommended full glass (6 to 8 oz) of water, and/or who continue to take oral bisphosphonates after developing symptoms suggestive of esophageal irritation. Therefore, it is very important that the full dosing instructions are provided to, and understood by, the patient (see Dosage and Administration [2.2]) . In patients who cannot comply with dosing instructions due to mental disability, therapy with ibandronate sodium tablets should be used under appropriate supervision.

There have been post-marketing reports of gastric and duodenal ulcers with oral bisphosphonate use, some severe and with complications, although no increased risk was observed in controlled clinical trials.

5.2 Hypocalcemia and Mineral Metabolism

Hypocalcemia has been reported in patients taking ibandronate sodium tablets. Treat hypocalcemia and other disturbances of bone and mineral metabolism before starting ibandronate sodium tablets therapy. Instruct patients to take supplemental calcium and vitamin D if their dietary intake is inadequate (see Dosage and Administration [2.3]) .

5.3 Musculoskeletal Pain

Severe and occasionally incapacitating bone, joint, and/or muscle pain has been reported in patients taking ibandronate sodium tablets and other bisphosphonates (see Adverse Reactions [6]) . The time to onset of symptoms varied from one day to several months after starting the drug. Most patients had relief of symptoms after stopping. A subset had recurrence of symptoms when rechallenged with the same drug or another bisphosphonate. Consider discontinuing use if severe symptoms develop.

5.4 Jaw Osteonecrosis

Osteonecrosis of the jaw (ONJ), which can occur spontaneously, is generally associated with tooth extraction and/or local infection with delayed healing, and has been reported in patients taking bisphosphonates, including ibandronate sodium. Known risk factors for osteonecrosis of the jaw include invasive dental procedures (e.g., tooth extraction, dental implants, boney surgery), diagnosis of cancer, concomitant therapies (e.g., chemotherapy, corticosteroids, angiogenesis inhibitors), poor oral hygiene, and co-morbid disorders (e.g., periodontal and/or other pre-existing dental disease, anemia, coagulopathy, infection, ill-fitting dentures). The risk of ONJ may increase with duration of exposure to bisphosphonates.

For patients requiring invasive dental procedures, discontinuation of bisphosphonate treatment may reduce the risk for ONJ. Clinical judgment of the treating physician and/or oral surgeon should guide the management plan of each patient based on individual benefit/risk assessment.

Patients who develop osteonecrosis of the jaw while on bisphosphonate therapy should receive care by an oral surgeon. In these patients, extensive dental surgery to treat ONJ may exacerbate the condition. Discontinuation of bisphosphonate therapy should be considered based on individual benefit/risk assessment.

5.5 Atypical Fractures Including Femoral Fractures

Atypical, low-energy, or low-trauma fractures of the femoral shaft have been reported during treatment with bisphosphonates including ibandronate in patients with osteoporosis. Atypical femur and other fractures most commonly occur with minimal or no trauma to the affected area. These fractures occurred anywhere in the femoral shaft from just below the lesser trochanter to above the supracondylar flare and are traverse or short oblique in orientation without evidence of comminution. Atypical fractures of other bones have also been reported. They may be bilateral. These fractures can also occur in osteoporotic patients who have not been treated with bisphosphonates. Concomitant treatment with glucocorticoids may also induce these fractures.

Prodromal pain in the affected area, usually presenting as dull, aching thigh pain, weeks to months before a complete fracture occurs was reported by patients.

Any patient with a history of bisphosphonate exposure who presents with thigh or groin pain should be suspected of having an atypical fracture and should be evaluated to rule out an incomplete femur fracture. Bony pain in other locations should also be considered for evaluation of atypical fracture. Patients presenting with an atypical fracture should also be assessed for symptoms and signs of fracture in the contralateral limb. Risk/benefit of continuing bisphosphonate therapy should be re-evaluated in these patients and interruption of bisphosphonate therapy should be considered.

5.6 Severe Renal Impairment

Ibandronate sodium tablets are not recommended for use in patients with severe renal impairment (creatinine clearance of less than 30 mL/min).

6 ADVERSE REACTIONS

The following clinically significant adverse drug reactions are described elsewhere in the labeling:

- Upper Gastrointestinal Adverse Reactions [see Warnings and Precautions (5.1)]
- Hypocalcemia and Mineral Metabolism [see Warnings and Precautions (5.2)]
- Musculoskeletal [see Warnings and Precautions (5.3)]
- Jaw Osteonecrosis [see Warnings and Precautions (5.4)]
- Atypical Fractures Including Femoral Fractures [see Warnings and Precautions (5.5)]
- Severe Renal Impairment [see Warnings and Precautions (5.6)]

6.1 Clinical Trials Experience

Because clinical trials are conducted under widely varying conditions, adverse reaction rates observed in the clinical trials of a drug cannot be directly compared to rates in the clinical trials of another drug and may not reflect the rates observed in practice.

Treatment and Prevention of Postmenopausal Osteoporosis

Daily Dosing

The safety of ibandronate sodium tablets 2.5 mg once daily in the treatment and prevention of postmenopausal osteoporosis was assessed in 3577 patients aged 41 – 82 years. The duration of the trials was 2 to 3 years, with 1134 patients exposed to placebo and 1140 exposed to ibandronate sodium tablets 2.5 mg. Patients with pre-existing gastrointestinal disease and concomitant use of non-steroidal anti-inflammatory drugs, proton pump inhibitors and H2 antagonists were included in these clinical trials. All patients received 500 mg calcium plus 400 international units vitamin D supplementation daily.

The incidence of all-cause mortality was 1% in the placebo group and 1.2% in the ibandronate sodium tablets 2.5 mg daily group. The incidence of serious adverse reactions was 20% in the placebo group and 23% in the ibandronate sodium tablets 2.5 mg daily group. The percentage of patients who withdrew from treatment due to adverse reactions was approximately 17% in both the ibandronate sodium tablets 2.5 mg daily group and the placebo group. Table 1 lists adverse reactions from the treatment and prevention studies reported in greater than or equal to 2% of patients and more frequently in patients treated daily with ibandronate sodium tablets than patients treated with placebo.

Table 1 Adverse Reactions Occurring at an Incidence Greater Than or Equal to 2% and in More Patients Treated with Ibandronate Sodium Tablets Than in Patients Treated with Placebo Daily in the Osteoporosis Treatment and Prevention Studies

Body System | Placebo%(n=1134) | Ibandronate Sodium Tablets 2.5 mg%(n=1140)
Body as a Whole
Back Pain | 12 | 14
Pain in Extremity | 6 | 8
Asthenia | 2 | 4
Allergic Reaction | 2 | 3
Digestive System
Dyspepsia | 10 | 12
Diarrhea | 5 | 7
Tooth Disorder | 2 | 4
Vomiting | 2 | 3
Gastritis | 2 | 2
Musculoskeletal System
Myalgia | 5 | 6
Joint Disorder | 3 | 4
Arthritis | 3 | 3
Nervous System
Headache | 6 | 7
Dizziness | 3 | 4
Vertigo | 3 | 3
Respiratory System
Upper Respiratory Infection | 33 | 34
Bronchitis | 7 | 10
Pneumonia | 4 | 6
Pharyngitis | 2 | 3
Urogenital System
Urinary Tract Infection | 4 | 6

Gastrointestinal Adverse Reactions

The incidence of selected gastrointestinal adverse reactions in the placebo and ibandronate sodium tablets 2.5 mg daily groups were: dyspepsia (10% vs. 12%), diarrhea (5% vs. 7%), and abdominal pain (5% vs. 6%).

Musculoskeletal Adverse Reactions

The incidence of selected musculoskeletal adverse reactions in the placebo and ibandronate sodium tablets 2.5 mg daily groups were: back pain (12% vs. 14%), arthralgia (14% vs. 14%) and myalgia (5% vs. 6%).

Ocular Adverse Events

Reports in the medical literature indicate that bisphosphonates may be associated with ocular inflammation such as iritis and scleritis. In some cases, these events did not resolve until the bisphosphonate was discontinued. There were no reports of ocular inflammation in studies with ibandronate sodium tablets 2.5 mg daily.

Monthly Dosing

The safety of ibandronate sodium tablets 150 mg once monthly in the treatment of postmenopausal osteoporosis was assessed in a two year trial which enrolled 1583 patients aged 54 to 81 years, with 395 patients exposed to ibandronate sodium tablets 2.5 mg daily and 396 exposed to ibandronate sodium tablets 150 mg monthly. Patients with active or significant pre-existing gastrointestinal disease were excluded from this trial. Patients with dyspepsia or concomitant use of non-steroidal anti-inflammatory drugs, proton pump inhibitors and H2 antagonists were included in this study. All patients received 500 mg calcium plus 400 international units vitamin D supplementation daily.

After one year, the incidence of all-cause mortality was 0.3% in both the ibandronate sodium tablets 2.5 mg daily group and the ibandronate sodium tablets 150 mg monthly group. The incidence of serious adverse events was 5% in the ibandronate sodium tablets 2.5 mg daily group and 7% in the ibandronate sodium tablets 150 mg monthly group. The percentage of patients who withdrew from treatment due to adverse events was 9% in the ibandronate sodium tablets 2.5 mg daily group and 8% in the ibandronate sodium tablets 150 mg monthly group. Table 2lists the adverse events reported in greater than or equal to 2% of patients.

Table 2 Adverse Events with an Incidence of at Least 2% in Patients Treated with Ibandronate Sodium Tablets 2.5 mg Daily or 150 mg Once-Monthly for Treatment of Postmenopausal Osteoporosis

Body System/Adverse Event | Ibandronate sodium tablets 2.5 mg Daily % (n=395) | Ibandronate sodium tablets 150 mg Monthly % (n=396)
Vascular Disorders
Hypertension | 7.3 | 6.3
Gastrointestinal Disorders
Dyspepsia | 7.1 | 5.6
Nausea | 4.8 | 5.1
Diarrhea | 4.1 | 5.1
Constipation | 2.5 | 4.0
Abdominal Paina | 5.3 | 7.8
Musculoskeletal and Connective Tissue Disorders
Arthralgia | 3.5 | 5.6
Back Pain | 4.3 | 4.5
Pain in Extremity | 1.3 | 4.0
Localized Osteoarthritis | 1.3 | 3.0
Myalgia | 0.8 | 2.0
Muscle Cramp | 2.0 | 1.8
Infections and Infestations
Influenza | 3.8 | 4.0
Nasopharyngitis | 4.3 | 3.5
Bronchitis | 3.5 | 2.5
Urinary Tract Infection | 1.8 | 2.3
Upper Respiratory Tract Infection | 2.0 | 2.0
Nervous System Disorders
Headache | 4.1 | 3.3
Dizziness | 1.0 | 2.3
General Disorders and Administration Site Conditions
Influenza-like Illnessb | 0.8 | 3.3
Skin and Subcutaneous Tissue Disorders
Rashc | 1.3 | 2.3
Psychiatric Disorders
Insomnia | 0.8 | 2.0

aCombination of abdominal pain and abdominal pain upper

bCombination of influenza-like illness and acute phase reaction

cCombination of rash pruritic, rash macular, rash papular, rash generalized, rash erythematous, dermatitis, dermatitis allergic, dermatitis medicamentosa, erythema and exanthema

Gastrointestinal Adverse Events

The incidence of adverse events in the ibandronate sodium tablets 2.5 mg daily and ibandronate sodium tablets 150 mg monthly groups were: dyspepsia (7% vs. 6%), diarrhea (4% vs. 5%), and abdominal pain (5% vs. 8%).

Musculoskeletal Adverse Events

The incidence of adverse events in the ibandronate sodium tablets 2.5 mg daily and ibandronate sodium tablets 150 mg monthly groups were: back pain (4% vs. 5%), arthralgia (4% vs. 6%) and myalgia (1% vs. 2%).

Acute Phase Reactions

Symptoms consistent with acute phase reactions have been reported with bisphosphonate use. Over the two years of the study, the overall incidence of acute phase reaction symptoms was 3% in the ibandronate sodium tablets 2.5 mg daily group and 9% in the ibandronate sodium tablets 150 mg monthly group. These incidence rates are based on the reporting of any of 33 acute-phase reaction like symptoms within 3 days of the monthly dosing and lasting 7 days or less. Influenza like illness was reported in no patients in the ibandronate sodium tablets 2.5 mg daily group and 2% in the ibandronate sodium tablets 150 mg monthly group.

Ocular Adverse Events

Two patients who received ibandronate sodium tablets 150 mg once-monthly experienced ocular inflammation, one was a case of uveitis and the other scleritis.

One hundred sixty (160) postmenopausal women without osteoporosis participated in a 1-year, double-blind, placebo-controlled study of ibandronate sodium tablets 150 mg once-monthly for prevention of bone loss. Seventy-seven subjects received ibandronate sodium tablets and 83 subjects received placebo. The overall pattern of adverse events was similar to that previously observed.

6.2 Postmarketing Experience

The following adverse reactions have been identified during postapproval use of ibandronate sodium tablets or bisphosphonate products. Because these reactions are reported voluntarily from a population of uncertain size, it is not always possible to reliably estimate their frequency or establish a causal relationship to drug exposure.

Hypersensitivity

Allergic reactions including anaphylactic reaction/shock with fatalities, angioedema, bronchospasm, asthma exacerbations, rash, Stevens-Johnson syndrome, erythema multiforme, and dermatitis bullous have been reported (see CONTRAINDICATIONS [4]) .

Hypocalcemia

Hypocalcemia has been reported in patients treated with ibandronate sodium tablets (see WARNINGS AND PRECAUTIONS [5.2]) .

Musculoskeletal

Bone, joint, or muscle pain, described as severe or incapacitating, has been reported rarely (see WARNINGS AND PRECAUTIONS [5.3]) ; low-energy femoral shaft and subtrochanteric fractures, and atypical fractures of other bones [see Warnings and Precautions (5.5)] .

Jaw Osteonecrosis

Osteonecrosis of the jaw and other oro-facial sites, including the external auditory canal, have been reported in patients treated with ibandronate sodium tablets (see WARNINGS AND PRECAUTIONS [5.4]) .

7 DRUG INTERACTIONS

7.1 Calcium Supplements/Antacids

Products containing calcium and other multivalent cations (such as aluminum, magnesium, iron) are likely to interfere with absorption of ibandronate sodium tablets. Therefore, instruct patients to take ibandronate sodium tablets at least 60 minutes before any oral medications, including medications containing multivalent cations (such as antacids, supplements or vitamins). Also, patients should wait at least 60 minutes after dosing before taking any other oral medications (see DOSAGE AND ADMINISTRATION [2.3]).

7.2 Aspirin/Nonsteroidal Anti-Inflammatory Drugs (NSAIDs)

Because aspirin, NSAIDs, and bisphosphonates are all associated with gastrointestinal irritation, caution should be exercised in the concomitant use of aspirin or NSAIDs with ibandronate sodium tablets.

7.3 H2 Blockers

In healthy volunteers, co-administration with ranitidine resulted in a 20% increased bioavailability of ibandronate, which was not considered to be clinically relevant (see CLINICAL PHARMACOLOGY [12.3]) .

7.4 Drug/Laboratory Test Interactions

Bisphosphonates are known to interfere with the use of bone-imaging agents. Specific studies with ibandronate have not been performed.

8 USE IN SPECIFIC POPULATIONS

8.1 Pregnancy

Risk Summary

Ibandronate sodium tablets is not indicated for use in women of reproductive potential. There are no data with ibandronate sodium use in pregnant women to inform any drug-associated risks.

In reproductive toxicity studies in the rat, ibandronate sodium caused post-implantation loss and obstruction of labor with maternal and fetal periparturient mortality at greater than or equal to 3 times human exposure at the recommended 2.5 mg daily oral dose, or at greater than or equal to 1 times human exposure at the recommended 150 mg once-monthly oral dose. In pregnant rats, kidney developmental toxicity occurred in offspring at greater than or equal to 30 times the daily 2.5 mg human dose or at greater than or equal to 9 times the once-monthly 150 mg human dose. In rat reproductive studies, impaired pup neuromuscular development was observed at 45 times the daily 2.5 mg dose and 13 times the once-monthly 150 mg dose. In reproductive studies in the rabbit, ibandronate sodium caused maternal mortality at greater than or equal to 8 times the daily 2.5 mg dose and greater than or equal to 4 times the once-monthly 150 mg dose (see Data).

Data

Animal Data
In female rats given ibandronate at oral doses greater than or equal to 3 times human exposure at the recommended daily oral dose of 2.5 mg or greater than or equal to 1 times human exposure at the recommended once-monthly oral dose of 150 mg beginning 14 days before mating and continuing through lactation, maternal deaths were observed at the time of delivery in all dose groups. Perinatal pup loss in dams given doses producing 45 times human exposure at the recommended daily dose and 13 times human exposure at the recommended once-monthly dose was likely related to maternal dystocia. Calcium supplementation did not completely prevent dystocia and periparturient mortality in any of the treated groups at greater than or equal to 16 times the recommended daily dose and greater than or equal to 4.6 times the recommended once-monthly dose. A low incidence of postimplantation loss was observed in rats treated from 14 days before mating throughout lactation or during gestation, only at doses causing maternal dystocia and periparturient mortality. In pregnant rats dosed orally from gestation day 17 through lactation day 21 (following closure of the hard palate through weaning), maternal toxicity, including dystocia and mortality, fetal perinatal and postnatal mortality, were observed at doses equivalent to human exposure at the recommended daily dose and greater than or equal to 4 times the recommended once-monthly dose. Periparturient mortality has also been observed with other bisphosphonates and appears to be a class effect related to inhibition of skeletal calcium mobilization resulting in hypocalcemia and dystocia.

Exposure of pregnant rats during the period of organogenesis resulted in an increased fetal incidence of RPU (renal pelvis ureter) syndrome at oral doses producing 30 times human exposure at the recommended daily oral dose of 2.5 mg and greater than or equal to 9 times human exposure at the recommended once-monthly oral dose of 150 mg. Impaired pup neuromuscular development (cliff avoidance test) was observed at 45 times human exposure at the daily dose and 13 times the once-monthly dose.

In pregnant rabbits treated orally with ibandronate during gestation at doses greater than or equal to 8 times the recommended human daily oral dose of 2.5 mg and greater than or equal to 4 times the recommended human once-monthly oral dose of 150 mg, dose-related maternal mortality was observed in all treatment groups. The deaths occurred prior to parturition and were associated with lung edema and hemorrhage. No significant fetal anomalies were observed.

Exposure multiples for the rat studies were calculated for the recommended daily oral dose of 2.5 mg or once-monthly dose of 150 mg based on area under the curve (AUC) comparison. Exposure multiples for the rabbit study were calculated for the recommended human daily oral dose of 2.5 mg or once-monthly dose of 150 mg based on dose/body surface area comparison. Doses used in pregnant animals were 1, 4, 5, 6, 16, 10, 20, 30, 60 or 100 mg/kg/day in rats, and 1, 4 or 20 mg/kg/day in rabbits.

8.2Lactation

Risk Summary

Ibandronate sodium tablets is not indicated for use in women of reproductive potential. There is no information on the presence of ibandronate in human milk, the effects of ibandronate on the breastfed infant, or the effects of ibandronate on milk production. Ibandronate is present in rat milk (see Data). The clinical relevance of these data is unclear.

Data

Animal Data

In lactating rats treated with intravenous doses of 0.08 mg/kg, ibandronate was present in breast milk from 2 to 24 hours after dose administration. Concentrations in milk averaged 1.5 times plasma concentrations.

8.4 Pediatric Use

Safety and effectiveness in pediatric patients have not been established.

8.5 Geriatric Use

Of the patients receiving ibandronate sodium tablets 2.5 mg daily in postmenopausal osteoporosis studies, 52% were over 65 years of age, and 10% were over 75 years of age. Of the patients receiving ibandronate sodium tablets 150 mg once-monthly in the postmenopausal osteoporosis 1-year study, 52% were over 65 years of age, and 9% were over 75 years of age. No overall differences in effectiveness or safety were observed between these patients and younger patients but greater sensitivity in some older individuals cannot be ruled out.

8.6 Renal Impairment

Ibandronate sodium tablets are not recommended for use in patients with severe renal impairment (creatinine clearance less than 30 mL/min).

10 OVERDOSAGE

No specific information is available on the treatment of overdosage of ibandronate sodium tablets. However, based on knowledge of this class of compounds, oral overdosage may result in hypocalcemia, hypophosphatemia, and upper gastrointestinal adverse events, such as upset stomach, dyspepsia, esophagitis, gastritis, or ulcer. Milk or antacids should be given to bind ibandronate sodium tablets. Due to the risk of esophageal irritation, vomiting should not be induced, and the patient should remain fully upright. Dialysis would not be beneficial.

11 DESCRIPTION

Ibandronate sodium is a nitrogen-containing bisphosphonate that inhibits osteoclast-mediated bone resorption. The drug substance used in ibandronate sodium tablets 150 mg is ibandronate sodium in the form of propylene glycol solvate. The chemical name for ibandronate sodium propylene glycol solvate is monosodium {1-hydroxy-3-[methyl(pentyl) amino]-1-phosphonopropyl} phosphonate propylene glycolate with the molecular formula C9H22NO7P2Na•C3H8O2and a molecular weight of 417.30. Ibandronate sodium propylene glycol solvate is a white to off-white powder. It is freely soluble in water and practically insoluble in organic solvents. Ibandronate sodium propylene glycol solvate has the following structural formula:

Ibandronate sodium tablets are available as white to off-white oval, biconvex, 150-mg film-coated tablets for once-monthly oral administration. One 150-mg film-coated tablet contains 196 mg of ibandronate sodium propylene glycol solvate, equivalent to 160.25 mg ibandronate sodium or to 150 mg of ibandronic acid. Ibandronate sodium tablets also contain the following inactive ingredients: microcrystalline cellulose, crospovidone, magnesium stearate, and colloidal silicon dioxide. The tablet film coating contains hypromellose, polyethylene glycol 8000, and purified water.

12 CLINICAL PHARMACOLOGY

12.1 Mechanism of Action

The action of ibandronate on bone tissue is based on its affinity for hydroxyapatite, which is part of the mineral matrix of bone. Ibandronate inhibits osteoclast activity and reduces bone resorption and turnover. In postmenopausal women, it reduces the elevated rate of bone turnover, leading to, on average, a net gain in bone mass.

12.2 Pharmacodynamics

Osteoporosis is characterized by decreased bone mass and increased fracture risk, most commonly at the spine, hip, and wrist. The diagnosis can be confirmed by a finding of low bone mass, evidence of fracture on x-ray, a history of osteoporotic fracture, or height loss or kyphosis indicative of vertebral fracture. While osteoporosis occurs in both men and women, it is most common among women following menopause. In healthy humans, bone formation and resorption are closely linked; old bone is resorbed and replaced by newly formed bone. In postmenopausal osteoporosis, bone resorption exceeds bone formation, leading to bone loss and increased risk of fracture. After menopause, the risk of fractures of the spine and hip increases; approximately 40% of 50-year-old women will experience an osteoporosis-related fracture during their remaining lifetimes.

Ibandronate sodium tablets produced biochemical changes indicative of dose-dependent inhibition of bone resorption, including decreases of biochemical markers of bone collagen degradation (such as deoxypyridinoline, and cross-linked C-telopeptide of Type I collagen) in the daily dose range of 0.25 mg to 5 mg and once-monthly doses from 100 mg to 150 mg in postmenopausal women.

Treatment with 2.5 mg daily ibandronate sodium tablets resulted in decreases in biochemical markers of bone turnover, including urinary C-terminal telopeptide of Type I collagen (uCTX) and serum osteocalcin, to levels similar to those in premenopausal women. Changes in markers of bone formation were observed later than changes in resorption markers, as expected, due to the coupled nature of bone resorption and formation. Treatment with 2.5 mg daily ibandronate sodium tablets decreased levels of uCTX within 1 month of starting treatment and decreased levels of osteocalcin within 3 months. Bone turnover markers reached a nadir of approximately 64% below baseline values by 6 months of treatment and remained stable with continued treatment for up to 3 years. Following treatment discontinuation, there is a return to pretreatment baseline rates of elevated bone resorption associated with postmenopausal osteoporosis.

In a 1-year, study comparing once-monthly vs. once-daily oral dosing regimens, the median decrease from baseline in serum CTX values was -76% for patients treated with the 150 mg once-monthly regimen and -67% for patients treated with the 2.5 mg daily regimen. In a 1-year, prevention study comparing ibandronate sodium tablets 150 mg once-monthly to placebo, the median placebo-subtracted decrease in sCTX was -49.8%.

12.3 Pharmacokinetics

Absorption

The absorption of oral ibandronate occurs in the upper gastrointestinal tract. Plasma concentrations increase in a dose-linear manner up to 50 mg oral intake and increases nonlinearly above this dose.

Following oral dosing, the time to maximum observed plasma ibandronate concentrations ranged from 0.5 to 2 hours (median 1 hour) in fasted healthy postmenopausal women. The mean oral bioavailability of 2.5 mg ibandronate was about 0.6% compared to intravenous dosing. The extent of absorption is impaired by food or beverages (other than plain water). The oral bioavailability of ibandronate is reduced by about 90% when ibandronate sodium tablets are administered concomitantly with a standard breakfast in comparison with bioavailability observed in fasted subjects. There is no meaningful reduction in bioavailability when ibandronate is taken at least 60 minutes before a meal. However, both bioavailability and the effect on bone mineral density (BMD) are reduced when food or beverages are taken less than 60 minutes following an ibandronate dose.

Distribution

After absorption, ibandronate either rapidly binds to bone or is excreted into urine. In humans, the apparent terminal volume of distribution is at least 90 L, and the amount of dose removed from the circulation via the bone is estimated to be 40% to 50% of the circulating dose. In vitroprotein binding in human serum was 99.5% to 90.9% over an ibandronate concentration range of 2 to 10 ng/mL in one study and approximately 85.7% over a concentration range of 0.5 to 10 ng/mL in another study.

Metabolism

Ibandronate does not undergo hepatic metabolism and does not inhibit the hepatic cytochrome P450 system. Ibandronate is eliminated by renal excretion. Based on a rat study, the ibandronate secretory pathway does not appear to include known acidic or basic transport systems involved in the excretion of other drugs. There is no evidence that ibandronate is metabolized in humans.

Elimination

The portion of ibandronate that is not removed from the circulation via bone absorption is eliminated unchanged by the kidney (approximately 50% to 60% of the absorbed dose). Unabsorbed ibandronate is eliminated unchanged in the feces.

The plasma elimination of ibandronate is multiphasic. Its renal clearance and distribution into bone accounts for a rapid and early decline in plasma concentrations, reaching 10% of the Cmaxwithin 3 or 8 hours after intravenous or oral administration, respectively. This is followed by a slower clearance phase as ibandronate redistributes back into the blood from bone. The observed apparent terminal half-life for ibandronate is generally dependent on the dose studied and on assay sensitivity. The observed apparent terminal half-life for the 150 mg ibandronate tablet upon oral administration to healthy postmenopausal women ranges from 37 to 157 hours.

Total clearance of ibandronate is low, with average values in the range 84 to 160 mL/min. Renal clearance (about 60 mL/min in healthy postmenopausal females) accounts for 50% to 60% of total clearance and is related to creatinine clearance. The difference between the apparent total and renal clearances likely reflects bone uptake of the drug.

Specific Populations

Pediatrics

The pharmacokinetics of ibandronate has not been studied in patients less than 18 years of age.

Geriatric

Because ibandronate is not known to be metabolized, the only difference in ibandronate elimination for geriatric patients versus younger patients is expected to relate to progressive age-related changes in renal function.

Gender

The bioavailability and pharmacokinetics of ibandronate are similar in both men and women.

Race

Pharmacokinetic differences due to race have not been studied.

Renal Impairment

Renal clearance of ibandronate in patients with various degrees of renal impairment is linearly related to creatinine clearance (CLcr).

Following a single dose of 0.5 mg ibandronate by intravenous administration, patients with CLcr 40 to 70 mL/min had 55% higher exposure (AUC∞) than the exposure observed in subjects with CLcr greater than 90 mL/min. Patients with CLcr less than 30 mL/min had more than a two-fold increase in exposure compared to the exposure for healthy subjects (see DOSAGE AND ADMINISTRATION [2.4]) .

Hepatic Impairment

No studies have been performed to assess the pharmacokinetics of ibandronate in patients with hepatic impairment because ibandronate is not metabolized in the human liver.

Drug Interaction Studies

Products containing calcium and other multivalent cations (such as aluminum, magnesium, iron), including milk, food, and antacids are likely to interfere with absorption of ibandronate, which is consistent with findings in animal studies.

H2 Blockers

A pharmacokinetic interaction study in healthy volunteers demonstrated that 75 mg ranitidine (25 mg injected intravenously 90 and 15 minutes before and 30 minutes after ibandronate administration) increased the oral bioavailability of 10 mg ibandronate by about 20%. This degree of increase is not considered to be clinically relevant.

13 NONCLINICAL TOXICOLOGY

13.1 Carcinogenesis, Mutagenesis, Impairment of Fertility

Carcinogenesis

In a 104-week carcinogenicity study, doses of 3, 7, or 15 mg/kg/day were administered by oral gavage to male and female Wistar rats (systemic exposures up to 12 and 7 times, respectively, human exposure at the recommended daily oral dose of 2.5 mg, and cumulative exposures up to 3.5 and 2 times, respectively, human exposure at the recommended once-monthly oral dose of 150 mg, based on AUC comparison). There were no significant drug-related tumor findings in male or female rats. In a 78-week carcinogenicity study, doses of 5, 20, or 40 mg/kg/day were administered by oral gavage to male and female NMRI mice (exposures up to 475 and 70 times, respectively, human exposure at the recommended daily oral dose of 2.5 mg and cumulative exposures up to 135 and 20 times, respectively, human exposure at the recommended once-monthly oral dose of 150 mg, based on AUC comparison). There were no significant drug-related tumor findings in male or female mice. In a 90-week carcinogenicity study, doses of 5, 20, or 80 mg/kg/day were administered in the drinking water to NMRI mice (cumulative monthly exposures in males and females up to 70 and 115 times, respectively, human exposure at the recommended dose of 150 mg, based on AUC comparison). A dose-related increased incidence of adrenal subcapsular adenoma/carcinoma was observed in female mice, which was statistically significant at 80 mg/kg/day (220 to 400 times human exposure at the recommended daily oral dose of 2.5 mg and 115 times human exposure at the recommended once-monthly oral dose of 150 mg, based on AUC comparison). The relevance of these findings to humans is unknown.

Mutagenesis

There was no evidence for a mutagenic or clastogenic potential of ibandronate in the following assays: in vitrobacterial mutagenesis assay in Salmonella typhimuriumand Escherichia coli(Ames test), mammalian cell mutagenesis assay in Chinese hamster V79 cells, and chromosomal aberration test in human peripheral lymphocytes, each with and without metabolic activation. Ibandronate was not genotoxic in the in vivomouse micronucleus tests for chromosomal damage.

Impairment of Fertility

In female rats treated from 14 days prior to mating through gestation, decreases in fertility, corpora lutea, and implantation sites were observed at an oral dose of 16 mg/kg/day (45 times human exposure at the recommended daily oral dose of 2.5 mg and 13 times human exposure at the recommended once-monthly oral dose of 150 mg, based on AUC comparison).

13.2 Animal Pharmacology

Animal studies have shown that ibandronate is an inhibitor of osteoclast-mediated bone resorption. In the Schenk assay in growing rats, ibandronate inhibited bone resorption and increased bone volume, based on histologic examination of the tibial metaphyses. There was no evidence of impaired mineralization at the highest dose of 5 mg/kg/day (subcutaneously), which is 1000 times the lowest antiresorptive dose of 0.005 mg/kg/day in this model, and 5000 times the optimal antiresorptive dose of 0.001 mg/kg/day in the aged ovariectomized rat. This indicates that ibandronate sodium tablets administered at therapeutic doses is unlikely to induce osteomalacia.

Long-term daily or once-monthly intermittent administration of ibandronate to ovariectomized rats or monkeys was associated with suppression of bone turnover and increases in bone mass. In both rats and monkeys, vertebral BMD, trabecular density, and biomechanical strength were increased dose-dependently at doses up to 15 times the recommended human daily oral dose of 2.5 mg, or cumulative monthly doses up to 8 times (rat) or 6 times (monkey) the recommended human once-monthly oral dose of 150 mg, based on body surface area (mg/m^2) or area under the curve (AUC) comparison. In monkeys, ibandronate maintained the positive correlation between bone mass and strength at the ulna and femoral neck. New bone formed in the presence of ibandronate had normal histologic structure and did not show mineralization defects.

14 CLINICAL STUDIES

14.1 Treatment of Postmenopausal Osteoporosis

Daily Dosing

The effectiveness and safety of ibandronate sodium tablets were demonstrated in a randomized, double-blind, placebo-controlled, multinational study (Treatment Study) of 2946 women aged 55 to 80 years, who were on average 21 years postmenopause, who had lumbar spine BMD 2 to 5 SD below the premenopausal mean (T-score) in at least one vertebra [L1 to L4], and who had 1 to 4 prevalent vertebral fractures. Ibandronate sodium tablets were evaluated at oral doses of 2.5 mg daily and 20 mg intermittently. The main outcome measure was the occurrence of new radiographically diagnosed vertebral fractures after 3 years of treatment. The diagnosis of an incident vertebral fracture was based on both qualitative diagnosis by the radiologist and quantitative morphometric criterion. The morphometric criterion required the dual occurrence of 2 events: a relative height ratio or relative height reduction in a vertebral body of at least 20%, together with at least a 4 mm absolute decrease in height. All women received 400 international units vitamin D and 500 mg calcium supplementation per day.

Effect on Fracture Incidence

Ibandronate sodium tablets 2.5 mg daily significantly reduced the incidence of new vertebral (primary efficacy measure) and of new and worsening vertebral fractures. Over the course of the 3-year study, the risk for vertebral fracture was 9.6% in the placebo-treated women and 4.7% in the women treated with ibandronate sodium tablets 2.5 mg (p<0.001) (see Table 3).

Table 3 Effect of Ibandronate Sodium Tablets on the Incidence of Vertebral Fracture in the 3-Year Osteoporosis Treatment Study*
 | Proportion of Patients with Fracture (%)
 | Placebo n=975 | Ibandronate sodium tablets 2.5 mg Daily n=977 | Absolute Risk Reduction (%) 95% CI | Relative Risk Reduction (%) 95% CI
New Vertebral Fracture | 9.6 | 4.7 | 4.9 | 52**
0-3 Year |  |  | (2.3, 7.4) | (29, 68)
New and Worsening Vertebral Fracture | 10.4 | 5.1 | 5.3 | 52
0-3 Year |  |  | (2.6, 7.9) | (30, 67)
Clinical (Symptomatic) Vertebral Fracture | 5.3 | 2.8 | 2.5 | 49
0-3 Year |  |  | (0.6, 4.5) | (14, 69)

* The endpoint value is the value at the study's last time point, 3 years, for all patients who had a fracture identified at that time; otherwise, the last postbaseline value prior to the study's last time point is used.

** p=0.0003 vs. placebo

Ibandronate sodium tablets 2.5 mg daily did not reduce the incidence of nonvertebral fractures (secondary efficacy measure). There was a similar number of nonvertebral osteoporotic fractures at 3 years reported in women treated with ibandronate sodium tablets 2.5 mg daily [9.1%, (95% CI: 7.1%, 11.1%)] and placebo [8.2%, (95% CI: 6.3%, 10.2%)]. The two treatment groups were also similar with regard to the number of fractures reported at the individual nonvertebral sites: pelvis, femur, wrist, forearm, rib, and hip.

Bone Mineral Density (BMD)

Ibandronate sodium tablets significantly increased BMD at the lumbar spine and hip relative to treatment with placebo. In the 3-year osteoporosis treatment study, ibandronate sodium tablets 2.5 mg daily produced increases in lumbar spine BMD that were progressive over 3 years of treatment and were statistically significant relative to placebo at 6 months and at all later time points. Lumbar spine BMD increased by 6.4% after 3 years of treatment with 2.5 mg daily ibandronate sodium tablets compared with 1.4% in the placebo group. Table 4displays the significant increases in BMD seen at the lumbar spine, total hip, femoral neck, and trochanter compared to placebo.

Table 4 Mean Percent Change in BMD from Baseline to Endpoint in Patients Treated Daily with Ibandronate Sodium Tablets 2.5 mg or Placebo in the 3-Year Osteoporosis Treatment Study [The endpoint value is the value at the study's last time point, 3 years, for all patients who had BMD measured at that time; otherwise, the last postbaseline value prior to the study's last time point is used.]
 | Placebo | Ibandronate sodium tablets 2.5 mg Daily
Lumbar Spine | 1.4 (n=693) | 6.4 (n=712)
Total Hip | -0.7 (n=638) | 3.1 (n=654)
Femoral Neck | -0.7 (n=683) | 2.6 (n=699)
Trochanter | 0.2 (n=683) | 5.3 (n=699)

Bone Histology

The effects of ibandronate sodium tablets 2.5 mg daily on bone histology were evaluated in iliac crest biopsies from 16 women after 22 months of treatment and 20 women after 34 months of treatment.

The histological analysis of bone biopsies showed bone of normal quality and no indication of osteomalacia or a mineralization defect.

Once-Monthly Dosing

The effectiveness and safety of ibandronate sodium tablets once-monthly were demonstrated in a randomized, double-blind, multinational, noninferiority trial in 1602 women aged 54 to 81 years, who were on average 18 years postmenopause, and had L2 to L4 lumbar spine BMD T-score below -2.5 SD at baseline. The main outcome measure was the comparison of the percentage change from baseline in lumbar spine BMD after 1 year of treatment with once-monthly ibandronate (100 mg, 150 mg) to daily ibandronate (2.5 mg). All patients received 400 international units vitamin D and 500 mg calcium supplementation per day.

Ibandronate sodium tablets 150 mg once-monthly (n=327) was shown to be noninferior to ibandronate sodium tablets 2.5 mg daily (n=318) in lumbar spine BMD in a 1-year, double-blind, multicenter study of women with postmenopausal osteoporosis. In the primary efficacy analysis (per-protocol population), the mean increases from baseline in lumbar spine BMD at 1 year were 3.86% (95% CI: 3.40%, 4.32%) in the 2.5 mg daily group and 4.85% (95% CI: 4.41%, 5.29%) in the 150 mg once-monthly group; the mean difference between 2.5 mg daily and 150 mg once-monthly was 0.99% (95% CI: 0.38%, 1.60%), which was statistically significant (p=0.002). The results of the intent-to-treat analysis were consistent with the primary efficacy analysis. The 150 mg once-monthly group also had consistently higher BMD increases at the other skeletal sites compared to the 2.5 mg daily group.

14.2 Prevention of Postmenopausal Osteoporosis

Daily Dosing

The safety and effectiveness of ibandronate sodium tablets 2.5 mg daily for the prevention of postmenopausal osteoporosis were demonstrated in a randomized, double-blind, placebo-controlled 2-year study (Prevention Study) of 653 postmenopausal women without osteoporosis at baseline. Women were aged 41 to 82 years, were on average 8.5 years postmenopause, and had lumbar spine BMD T-scores greater than -2.5. Women were stratified according to time since menopause (1 to 3 years, greater than 3 years) and baseline lumbar spine BMD (T-score: greater than -1, -1 to -2.5). The study compared daily ibandronate sodium tablets at three dose levels (0.5 mg, 1.0 mg, 2.5 mg) with placebo. All women received 500 mg of supplemental calcium per day.

The primary efficacy measure was the change in BMD of lumbar spine after 2 years of treatment. Ibandronate sodium tablets 2.5 mg daily resulted in a mean increase in lumbar spine BMD of 3.1% compared with placebo following 2 years of treatment. Increases in BMD were seen at 6 months and at all later time points. Irrespective of the time since menopause or the degree of pre-existing bone loss, treatment with ibandronate sodium tablets resulted in a higher BMD response at the lumbar spine compared with placebo across all four baseline strata [time since menopause (1 to 3 years, greater than 3 years) and baseline lumbar spine BMD (T-score: greater than -1, -1 to -2.5)].

Compared with placebo, treatment with ibandronate sodium tablets 2.5 mg daily increased BMD of the total hip by 1.8%, the femoral neck by 2.0%, and the trochanter by 2.1%.

Once-Monthly Dosing

The safety and effectiveness of ibandronate sodium tablets 150 mg once-monthly for the prevention of postmenopausal osteoporosis were demonstrated in a randomized, double-blind, placebo-controlled 1-year study (Monthly Prevention Study) of 160 postmenopausal women with low bone mass at baseline (T-score of -1 to -2.5). Women, aged 46 to 60 years, were on average 5.4 years postmenopause. All women received 400 international units of vitamin D and 500 mg calcium supplementation daily.

The primary efficacy measure was the relative change in BMD at the lumbar spine after 1 year of treatment. Ibandronate sodium tablets 150 mg once-monthly resulted in a mean increase in lumbar spine BMD of 4.12% (95% confidence interval 2.96 to 5.28) compared with placebo following 1 year of treatment (p<0.0001), based on a 3.73% and -0.39% mean change in BMD from baseline in the 150 mg once-monthly ibandronate sodium tablets and placebo treatment groups, respectively. BMD at other skeletal sites was also increased relative to baseline values.

16 HOW SUPPLIED/STORAGE AND HANDLING

16.1 How Supplied

Ibandronate sodium 150-mg tablets are supplied as white to off-white, oval, biconvex, film-coated tablets, engraved with "APO" on one side and "IBA150" on the other side. They are supplied as follows:

Packaged in bundles of 3 boxes, each box containing 1 blister strip of 1 tablet each (NDC 60429-643-73).

16.2 Storage and Handling

Store at 20° to 25°C (68° to 77°F); excursions permitted between 15° and 30°C (59° and 86°F) [see USP Controlled Room Temperature].

Dispense in a tight container [see USP].

17 PATIENT COUNSELING INFORMATION

"See FDA-approved patient labeling (Medication Guide)"

17.1 Information for Patients

Instruct patients to read the Medication Guide carefully before taking ibandronate sodium tablets and to re-read it each time the prescription is renewed because it contains important information the patient should know about ibandronate sodium tablets The Medication Guide also includes the dosing instructions in order to maximize absorption and clinical benefit.

- Ibandronate sodium tablets should be taken at least 60 minutes before the first food or drink (other than water) of the day and before taking any oral medication or supplementation including calcium, antacids or vitamins (see DRUG INTERACTIONS [7.1]) .
- To facilitate delivery to the stomach, and thus reduce the potential for esophageal irritation, ibandronate sodium tablets should be swallowed whole with a full glass of plain water (6 to 8 oz) while the patient is standing or sitting in an upright position. Patients should not lie down for 60 minutes after taking ibandronate sodium tablets.
- Patients should not eat, drink anything except for water, or take other medications for 60 minutes after taking ibandronate sodium tablets.
- Plain water is the only drink that should be taken with ibandronate sodium tablets. Note that some mineral waters may have a higher concentration of calcium and therefore should not be used.
- Patients should not chew or suck the tablet because of a potential for oropharyngeal ulceration.
- The ibandronate sodium tablets 150 mg tablet should be taken on the same date each month (i.e., the patient’s ibandronate sodium tablets day).
- The patient must not take two 150 mg tablets within the same week.
- If the once-monthly dose is missed, and the patient’s next scheduled ibandronate sodium tablets day is more than 7 days away, the patient should be instructed to take one ibandronate sodium 150 mg tablet in the morning following the date that it is remembered (see DOSAGE AND ADMINISTRATION [2.3]) . The patient should then return to taking one ibandronate sodium 150 mg tablet every month in the morning of their chosen day, according to their original schedule.
- If the once-monthly dose is missed, and the patient’s next scheduled ibandronate sodium tablets day is only 1 to 7 days away, the patient must wait until the subsequent month’s scheduled ibandronate sodium tablets day to take their tablet. The patient should then return to taking one ibandronate sodium 150 mg tablet every month in the morning of their chosen day, according to their original schedule.

Patients should receive supplemental calcium and vitamin D if dietary intake is inadequate. Intake of supplemental calcium and vitamin D should be delayed for at least 60 minutes following oral administration of ibandronate sodium tablets in order to maximize absorption of ibandronate sodium tablets.

Physicians should be alert to signs or symptoms signaling a possible esophageal reaction during therapy, and patients should be instructed to discontinue ibandronate sodium tablets and seek medical attention if they develop symptoms of esophageal irritation such as new or worsening dysphagia, pain on swallowing, retrosternal pain, or heartburn.

APOTEX INC.
IBANDRONATE SODIUM TABLETS
150 mg

Manufactured by | Manufactured for
Apotex Inc. | Apotex Corp.
Toronto, Ontario | Weston, Florida
Canada M9L 1T9 | 33326

Rev. 20

Marketed by:
GSMS, Inc.
Camarillo, CA 93012 USA

MEDICATION GUIDE

Ibandronate Sodium (eye-ban-droe-nate soe-dee-um)Tablets

Read the Medication Guide that comes with ibandronate sodium tablets before you start taking it and each time you get a refill. There may be new information. This Medication Guide does not take the place of talking with your doctor about your medical condition or your treatment. Talk to your doctor if you have any questions about ibandronate sodium tablets.

What is the most important information I should know about ibandronate sodium tablets?

Ibandronate sodium tablets may cause serious side effects including:

1. Esophagus problems

2. Low calcium levels in your blood (hypocalcemia)

3. Bone, joint or muscle pain

4. Severe jaw bone problems (osteonecrosis)

5. Unusual bone fractures including thigh bone fractures

1. Esophagus problems.

Some people who take ibandronate sodium tablets may develop problems in the esophagus (the tube that connects the mouth and the stomach). These problems include irritation, inflammation, or ulcers of the esophagus which may sometimes bleed.

• It is important that you take ibandronate sodium tablets exactly as prescribed to help lower your chance of getting esophagus problems (see the section “How should I take ibandronate sodium tablets?”).

• Stop taking ibandronate sodium tablets and call your doctor right away if you get chest pain, new or worsening heartburn, or have trouble or pain when you swallow.

2. Low calcium levels in your blood (hypocalcemia).

Ibandronate sodium tablets may lower the calcium levels in your blood. If you have low blood calcium before you start taking ibandronate sodium tablets, it may get worse during treatment. Your low blood calcium must be treated before you take ibandronate sodium tablets. Most people with low blood calcium levels do not have symptoms, but some people may have symptoms. Call your doctor right away if you have symptoms of low blood calcium such as:

• Spasms, twitches, or cramps in your muscles

• Numbness or tingling in your fingers, toes, or around your mouth

Your doctor may prescribe calcium and vitamin D to help prevent low calcium levels in your blood, while you take ibandronate sodium tablets. Take calcium and vitamin D as your doctor tells you to.

3. Bone, joint, or muscle pain.

Some people who take ibandronate sodium tablets develop severe bone, joint, or muscle pain.

4. Severe jaw bone problems (osteonecrosis).

Severe jaw bone problems may happen when you take ibandronate sodium tablets. Your doctor may examine your mouth before you start ibandronate sodium tablets. Your doctor may tell you to see your dentist before you start ibandronate sodium tablets. It is important for you to practice good mouth care during treatment with ibandronate sodium tablets.

5. Unusual breaks in thigh and other bones.

Some people have had unusual bone breaks, including thigh bone, when taking ibandronate sodium tablets. A break in the thigh bone can feel like a new pain in your hip, groin, or thigh. People taking ibandronate sodium tablets can also have breaks in other bones.

Call your doctor right away if you have any of these side effects.

What are ibandronate sodium tablets?

Ibandronate sodium tablets are a prescription medicine used to treat or prevent osteoporosis in women after menopause. Ibandronate sodium tablets help increase bone mass and helps reduce the chance of having a spinal fracture (break).

It is not known how long ibandronate sodium tablets works for the treatment and prevention of osteoporosis. You should see your doctor regularly to determine if ibandronate sodium tablets are still right for you.

It is not known if ibandronate sodium tablets are safe and effective in children.

Who should not take ibandronate sodium tablets?

Do not take ibandronate sodium tablets if you:

• Have certain problems with your esophagus, the tube that connects your mouth with your stomach

• Cannot stand or sit upright for at least 60 minutes

• Have low levels of calcium in your blood

• Are allergic to ibandronate sodium tablets or any of its ingredients. A list of ingredients is at the end of this leaflet

What should I tell my doctor before taking ibandronate sodium tablets?

Before you start ibandronate sodium tablets, be sure to talk to your doctor if you:

• Have problems with swallowing

• Have stomach or digestive problems

• Have low blood calcium

• Plan to have dental surgery or teeth removed

• Have kidney problems

• Have been told you have trouble absorbing minerals in your stomach or intestines (malabsorption syndrome)

• Are pregnant, or plan to become pregnant. It is not known if ibandronate sodium tablets can harm your unborn baby.

• Are breast-feeding or plan to breast-feed. It is not known if ibandronate sodium passes into your milk and may harm your baby.

Tell your doctor and dentist about all the medicines you take,including prescription and non-prescription medicines, vitamins, and herbal supplements. Certain medicines may affect how ibandronate sodium tablets works.

Especially tell your doctor if you take:

• antacids

• aspirin

• Nonsteroidal Anti-Inflammatory (NSAID) medicines

Know the medicines you take. Keep a list of them and show it to your doctor and pharmacist each time you get a new medicine.

How should I take ibandronate sodium tablets?

• Take ibandronate sodium tablets exactly as your doctor tells you.

• Take 1 ibandronate sodium tablets 150 mg tablet 1 time every month on the same day each month.

• Ibandronate sodium tablets work only if taken on an empty stomach.

• Take 1 ibandronate sodium tablet, afteryou get up for the day and beforetaking your first food, drink, or other medicine.

• Take ibandronate sodium tablets while you are sitting or standing.

• Do not chew or suck on a tablet of ibandronate sodium tablets.

• Swallow ibandronate sodium tablet with a full glass (6 to 8 oz) of plain wateronly.

• Do nottake ibandronate sodium tablets with mineral water, coffee, tea, soda, or juice.

After swallowing ibandronate sodium tablet, wait at least 60 minutes:

• Before you lie down. You may sit, stand or walk, and do normal activities like reading.

• Before you take your first food or drink except for plain water.

• Before you take other medicines, including antacids, calcium, and other supplements and vitamins.

Do not lie down for at least 60 minutes after you take ibandronate sodium tablets and do not eat your first food of the day for at least 60 minutes after you take ibandronate sodium tablets.

If you miss a dose of ibandronate sodium tablets, do not take it later in the day. Call your doctor for instructions.

If you take too much ibandronate sodium tablets, call your doctor. Do not try to vomit. Do not lie down.

What are the possible side effects of ibandronate sodium tablets?

Ibandronate sodium tablets may cause serious side effects.

• See “What is the most important information I should know about ibandronate sodium tablets?”

The most common side effects of ibandronate sodium tablets are:

• Back pain

• Heartburn

• Stomach area (abdominal) pain

• Pain in your arms and legs

• Diarrhea

• Headache

• Muscle pain

• Flu-like symptoms

You may get allergic reactions, such as hives, breathing difficulties, swelling of your face, lips, tongue or throat, or feeling faint.

Tell your doctor if you have any side effect that bothers you or that does not go away.

These are not all the possible side effects of ibandronate sodium tablets. For more information, ask your doctor or pharmacist.

Call your doctor for medical advice about side effects. You may report side effects to FDA at 1-800-FDA-1088.

How do I store ibandronate sodium tablets?

• Store ibandronate sodium tablets at room temperature, 59°F to 86°F (15°C to 30°C).

• Keep ibandronate sodium tablets in a tightly closed container.

Keep ibandronate sodium tablets and all medicines out of the reach of children.

General information about the safe and effective use of ibandronate sodium tablets.

Medicines are sometimes prescribed for purposes other than those listed in a Medication Guide. Do not use ibandronate sodium tablets for a condition for which it was not prescribed. Do not give ibandronate sodium tablets to other people, even if they have the same symptoms you have. It may harm them.

This Medication Guide summarizes the most important information about ibandronate sodium tablets.

If you would like more information, talk with your doctor.

You can ask your doctor or pharmacist for information about ibandronate sodium tablets that is written for health professionals.

For more information, go to www.apotex.com or call 1-800-706-5575

What are the ingredients of ibandronate sodium tablets?

Active ingredient: ibandronate sodium

Inactive ingredients: microcrystalline cellulose, crospovidone, magnesium stearate, and colloidal silicon dioxide. The tablet film coating contains hypromellose, polyethylene glycol 8000 and purified water.

This Medication Guide has been approved by the U.S. Food and Drug Administration

INSTRUCTIONS FOR OPENING:

1. Peel back the plastic tab on the blister card to completely remove the paper-foil layer that covers the tablet

Ensure that the paper-foil layer is completely removed from the area over tablet.

2. With clean and dry hands, carefully remove the tablet.

APOTEX INC.
IBANDRONATE SODIUM TABLETS
150 mg

Manufactured by | Manufactured for
Apotex Inc. | Apotex Corp.
Toronto, Ontario | Weston, Florida
Canada M9L 1T9 | 33326

Revised: January 2026

Rev. 20

Marketed by:
GSMS, Inc.
Camarillo, CA 93012 USA

PRINCIPAL DISPLAY PANEL - 150 mg CARTON LABEL

NDC No. 60429-643-73

Ibandronate Sodium Tablet

Each tablet contains 196 mg of ibandronate sodium propylene glycol solvate equivalent to 160.25 mg ibandronate sodium or 150 mg of ibandronic acid.

150 mg

Rx Only

1 tablet